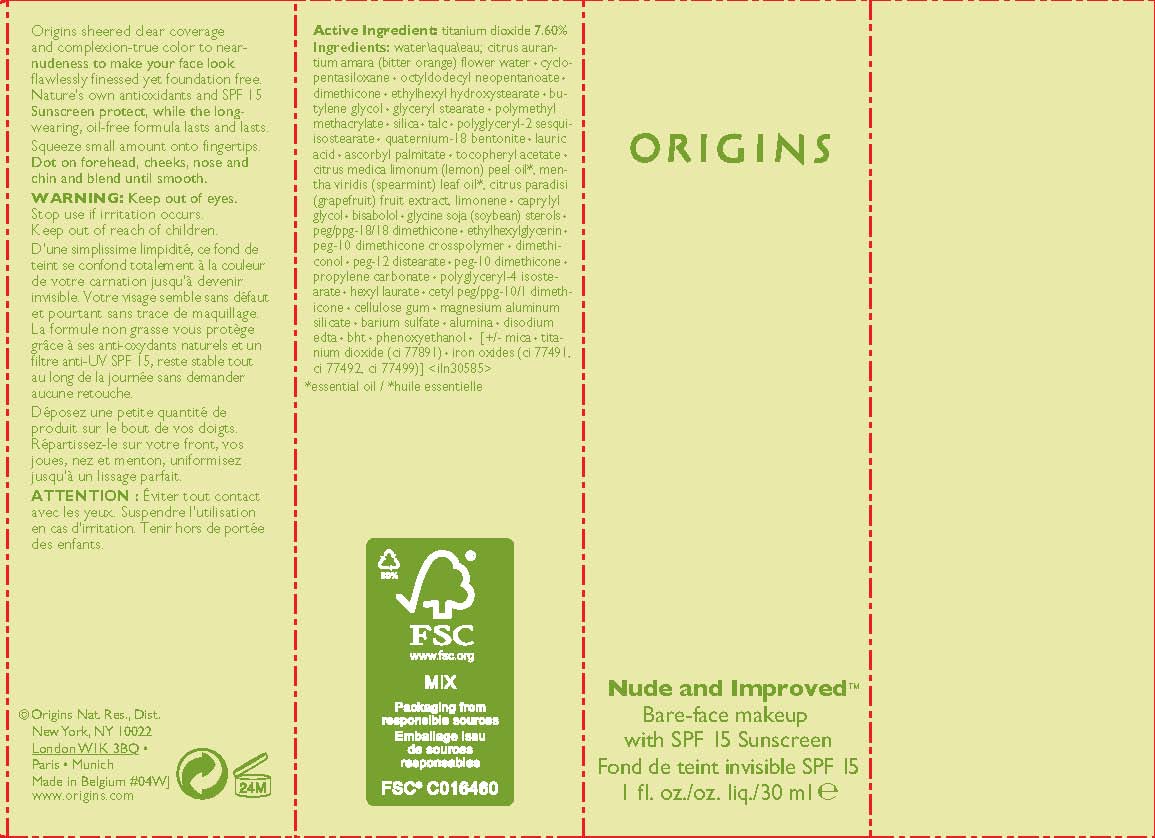 DRUG LABEL: NUDE AND IMPROVED BARE FACE MAKEUP
NDC: 59427-761 | Form: LOTION
Manufacturer: ORIGINS NATURAL RESOURCES INC.
Category: otc | Type: HUMAN OTC DRUG LABEL
Date: 20110728

ACTIVE INGREDIENTS: TITANIUM DIOXIDE 7.6 mL/100 mL
INACTIVE INGREDIENTS: WATER; CYCLOMETHICONE 5; OCTYLDODECYL NEOPENTANOATE; DIMETHICONE; ETHYLHEXYL HYDROXYSTEARATE; BUTYLENE GLYCOL; GLYCERYL MONOSTEARATE; SILICON DIOXIDE; TALC; LAURIC ACID; ASCORBYL PALMITATE; CITRUS AURANTIUM FLOWER OIL; CAPRYLYL GLYCOL; LEVOMENOL; SOY STEROL; ETHYLHEXYLGLYCERIN; DIMETHICONOL (250000 MW); PEG-12 STEARATE; PROPYLENE CARBONATE; POLYGLYCERYL-4 ISOSTEARATE; HEXYL LAURATE; CARBOXYMETHYLCELLULOSE SODIUM; BARIUM SULFATE; ALUMINUM OXIDE; EDETATE DISODIUM; BUTYLATED HYDROXYTOLUENE; PHENOXYETHANOL; FERROUS OXIDE

active ingredient: titanium dioxide 7.60%

INACTIVE INGREDIENT

inactive ingredients: water\aqua\eau; citrus aurantium amara (bitter orange) flower water [] cyclopentasiloxane [] octyldodecyl neopentanoate [] dimethicone [] ethylhexyl hydroxystearate [] butylene glycol [] glyceryl stearate [] polymethyl methacrylate [] silica [] talc [] polyglyceryl-2 sesquiisostearate [] quaternium-18 bentonite [] lauric acid [] ascorbyl palmitate [] tocopheryl acetate [] citrus medica limonum (lemon) peel oil*, mentha viridis (spearmint) leaf oil*, citrus paradisi (grapefruit) fruit extract, limonene [] caprylyl glycol [] bisabolol [] glycine soja (soybean) sterols [] peg/ppg-18/18 dimethicone [] ethylhexylglycerin [] peg-10 dimethicone crosspolymer [] dimethiconol [] peg-12 distearate [] peg-10 dimethicone [] propylene carbonate [] polyglyceryl-4 isostearate [] hexyl laurate [] cetyl peg/ppg-10/1 dimethicone [] cellulose gum [] magnesium aluminum silicate [] barium sulfate [] alumina [] disodium edta [] bht [] phenoxyethanol [] [+/- mica [] titanium dioxide (ci 77891) [] iron oxides (ci 77491, ci 77492, ci 77499)]

WARNINGS

warning: keep out of eyes. stop use if irritation occurs. keep out of reach of children

PACKAGE LABEL

principal display panel:

ORIGINS

NUDE AND IMPROVED

BARE-FACE MAKEUP

WITH SPF 15

SUNSCREEN

1 fl oz liq/30 ml

origins natural resources inc

new york, ny 10022